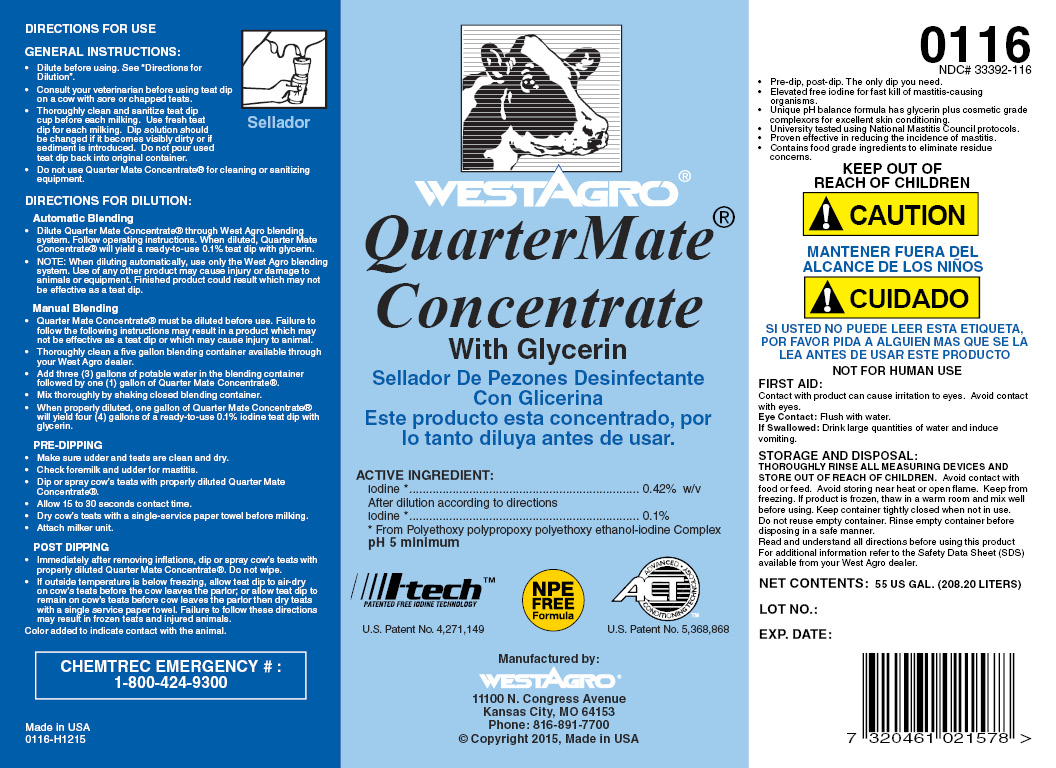 DRUG LABEL: QuarterMate Concentrate
NDC: 33392-116 | Form: SOLUTION, CONCENTRATE
Manufacturer: WestAgro, Inc.
Category: animal | Type: OTC ANIMAL DRUG LABEL
Date: 20211213

ACTIVE INGREDIENTS: IODINE 4.38 g/1 L
INACTIVE INGREDIENTS: SODIUM HYDROXIDE; ANHYDROUS CITRIC ACID; GLYCERIN; XANTHAN GUM; POLOXAMER 335; POLOXAMER 403; DOCUSATE SODIUM; SODIUM IODIDE; WATER

WESTAGRO
QuarterMate Concentrate with Glycerin

INDICATIONS AND USAGE

DIRECTIONS FOR USE:

GENERAL INSTRUCTIONS

- Dilute before using. See "Directions for Dilution".
- Consult your veterinarian before using teat dip on a cow with sore or chapped teats.
- Thoroughly clean and sanitize teat dip cup before each milking. Use fresh teat dip for each milking. Dip solution should be changed if it becomes visibly dirty or if sediment is introduced. Do not pour used teat dip back into original container.
- Do not use Quarter Mate Concentrate for cleaning or sanitizing equipment.

DIRECTIONS FOR DILUTION

Automatic blending

- Dilute Quarter Mate Concentrate through a West Agro blending system. Follow operating instructions. When diluted, Quarter Mate Concentrate will yield a ready-to-use 0.1% iodine teat dip with glycerin.

- NOTE: When diluting automatically, use only the West Agro blending delivery system. Use of any other product may cause injury or damage to animals or equipment. Finished product could result which may not be effective as a teat dip.

Manual Blending

- Quarter Mate Concentrate must be diluted before use. Failure to follow the following instructions may result in a product which may not be effective as a teat dip or which may cause injury to animal.
- Thoroughly clean a five gallon blending container available through your West Agro dealer.
- Add three (3) gallons of potable water in the blending container followed by one (1) gallon of Quarter Mate Concentrate.
- Mix thoroughly by shaking closed blending container.
- When properly diluted, one gallon of Quarter Mate Concentrate will yield four (4) gallons of a ready-to-use 0.1% iodine teat dip with glycerin.

PRE-DIPPING

- Make sure udder and teats are clean and dry.
- Check milk and udder for mastitis.
- Dip or spray cow's teats with properly diluted Quarter Mate Concentrate.
- Allow 15 to 30 seconds contact time.
- Dry cow's teats with a single service paper towel before milking.
- Attach milker unit.

POST-DIPPING

- Immediately after removing inflations, dip or spray cow's teats with properly diluted Quarter Mate Dip Concentrate. Do not wipe.
- If outside temperature is below freezing, allow teat dip to air-dry on cow's teats before cow leaves the parlor; or allow teat dip to remain on cow's teats before cow leaves the parlor then dry teats with a single service paper towel. Failure to follow these directions may result in frozen teats and injured animals.

Color added to indicate contact with the animal.

Made in U.S.A.

0116-E0405

Copyright 2005, West Agro, Inc.

WestAgro

QuarterMate Concentrate

With Glycerin

Sellador De Pezones Desinfectante Con Glicerina

Este producto esta concentrado, por lo tanto diluya antes de usar.

ACTIVE INGREDIENT:
Iodine ......................................... 0.42% w/v
After dilution according to directions
Iodine ......................................... 0.1%

From polyethoxy polypropoxy polyethoxy ethanol-iodine complex
pH 5 minumum

I-tech
PATENTED FREE IODINE TECHNOLOGY
U.S. Patent No 4,271,149

NPE FREE Formula

ACT
ADVANCED CONDITIONING TECHNOLOGY

U.S. Patent No.
5,368,868

Manufactured by:
WESTAGRO
11100 N. Congress Ave. Kansas City, MO
63153-1296

0116

NDC 33392-116

- Pre-dip, post-dip, the only dip you need.
- Elevated free iodine for fast kill of mastitis causing organisms.
- Unique pH balance formula has glycerin plus cosmetic grade complexors for excellent skin conditioning.
- University tested using National Mastitis Council protocols. Proven effective in reducing the incidence of mastitis.
- Contains food grade ingredients to eliminate residue concerns.

KEEP OUT OF REACH OF CHILDREN

! CAUTION

MANTENER FUERA DEL ALCANCE DE LOST NINOS

! CUIDADO

SI USTED NO PURDE LEER ESTA ETIQUETA, POR FAVOR PIDA A ALGUIEN MAS QUE SE LA LEA ANTES DE USAR ESTE PRODUCTO

FIRST AID
Contact with product can cause irritation to eyes.
Avoid contact with eyes.
Eye Contact: Flush with water.
If Swallowed: Drink large quantities of water and induce vomiting.

STORAGE AND DISPOSAL

THOROUGHLY RINSE ALL MEASURING DEVICES AND STORE OUT OF REACH OF CHILDREN. Avoid contact with food or feed. Avoid storing near heat or open flame. Keep from freezing. If product is frozen, thaw in a warm room and mix well before using. Keep container tightly closed when not in use. Do not reuse empty container.

Rinse empty container before disposing in a safe manner.

Read and understand all directions before using this product. For additional information refer to the Material Safety Data Sheet (MSDS) available from your West Agro dealer.

CHEMTREC EMERGENCY No. 1-800-424-9300

NET
CONTENTS:

LOT NO:

EXPIRATION DATE: